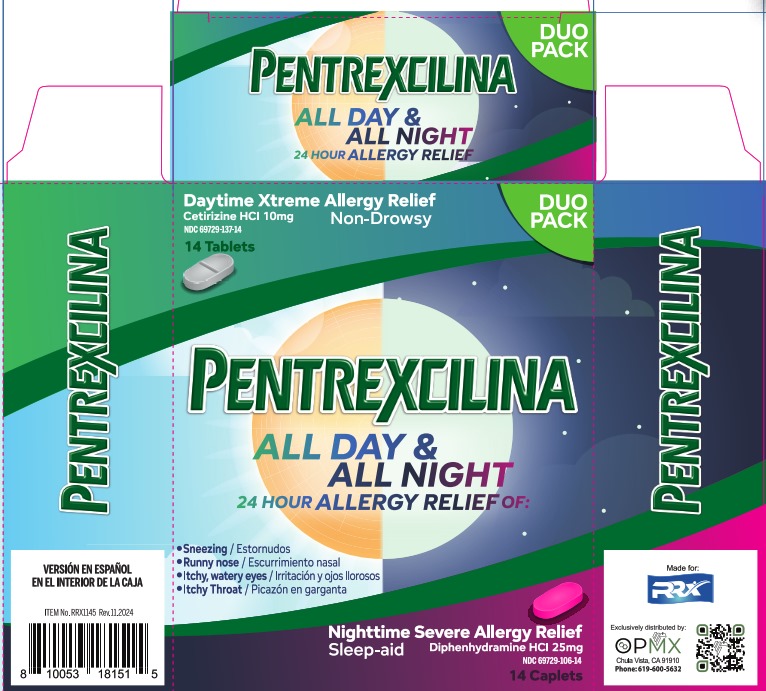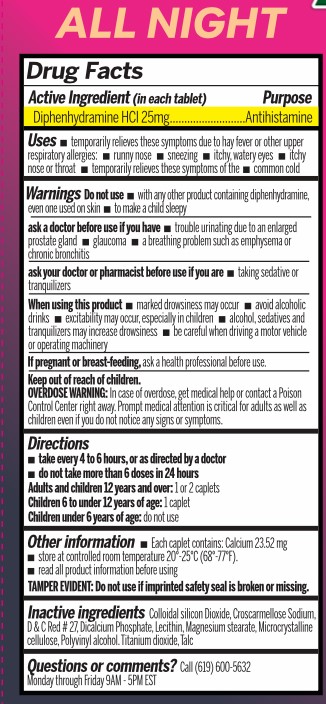 DRUG LABEL: Pentrexcilina Severe Allergy
NDC: 69729-106 | Form: TABLET, FILM COATED
Manufacturer: OPMX LLC
Category: otc | Type: HUMAN OTC DRUG LABEL
Date: 20241115

ACTIVE INGREDIENTS: DIPHENHYDRAMINE HYDROCHLORIDE 25 mg/1 1
INACTIVE INGREDIENTS: MAGNESIUM STEARATE; ANHYDROUS DIBASIC CALCIUM PHOSPHATE; D&C RED NO. 27; MICROCRYSTALLINE CELLULOSE; POLYVINYL ALCOHOL, UNSPECIFIED; TALC; TITANIUM DIOXIDE; LECITHIN, SOYBEAN; SILICON DIOXIDE; CROSCARMELLOSE SODIUM

Pentrexcilina Night Time

Drug Facts

Active ingredient (in each tablet)

Diphenhydramine HCl 25mg

Purpose

Antihistamine

Uses

temporarily relieves these symptoms due to hay fever or other upper respiratory allergies:

- runny nose
- sneezing
- itchy, watery eyes
- itchy nose or throat
- temporarily relieves these symptoms of the
- common cold

Warnings

Do not use

- with any other product containing dyphenhydramine, even one used on skin
- to make a child sleepy

ask a doctor before use if you have

- trouble urinating due to an enlarged prostate gland
- a breathing problem such as emphysema or chronic bronchitis

ask your doctor or pharmacist before use if you are

- taking sedative or tranquilizers

When using this product

- marked drowsiness may occur
- avoid alcoholic drinks
- excitability may occur, especially in children
- alcohol, sedatives and tranquilizers may increase drowsiness
- be careful when driving a motor vehicle or operating machinery

If pregnant or breast-feeding,

ask a professional before use

OVERDOSE WARNING

In case of overdose, get medical help or contact a Poison Control Center right away. Prompt medical attention is critical for adults as well as children even if you do not notice any signs or symptoms.

Directions

- take every 4 to 6 hours, or as directed by a doctor
- do not take more than 6 doses in 24 hours

Adults and children 12 years and over: 1 or 2 caplets

Children 6 to under 12 years of age: 1 caplet

Children under 6 years of age: do not use

Other information

- Each caplet contains: Calcium 23.52 mg
- store at controlled room temperature 20°-25°C (68°-77°F).
- read all product information before using

TAMPER EVIDENT: Do not use if imprinted safety seal is broken or missing.

Inactive ingredients

Colloidal silicon Dioxide, Croscarmellose Sodium, D & C Red #27, Dicalcium Phosphate, Lecithin, Magnesium stearate, Microcrystalline cellulose, Polyvinyl alcohol, Titanium dioxide, Talc.

Questions or comments?

Call (619) 600-5632

Monday through Friday 9AM- 5PM EST

Principal display Panel

Daytime Xtreme Allergy Relief

Cetirizine HCl 10mg

Non-Drowsy

NDC 69729-137-14

14 Tablets

DUO PACK

PENTREXCILINA

ALL DAY & ALL NIGHT

24 HOUR ALLERGY RELIEF OF:

Sneezing/ Estornudos
Runny nose/ Escurrimiento nasal
Itchy, watery eyes/ Irritación y ojos llorosos
Itchy throat/ Picazón en garganta

Nighttime Severe Allergy Relief

Sleep-aid

Diphenhydramine HCl 25mg

NDC 69729-106-14

14 Caplets

Made for RRX

Exclusively distributed by:

OPMX

Chula Vista CA 91910

Phone: 619-600-5632